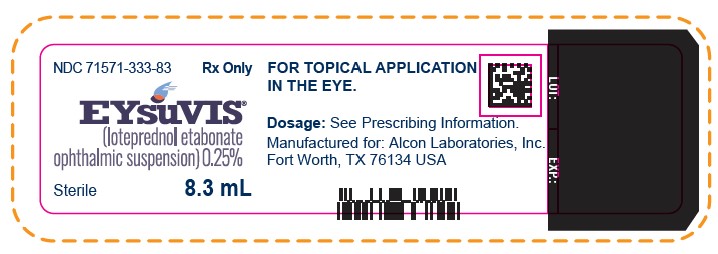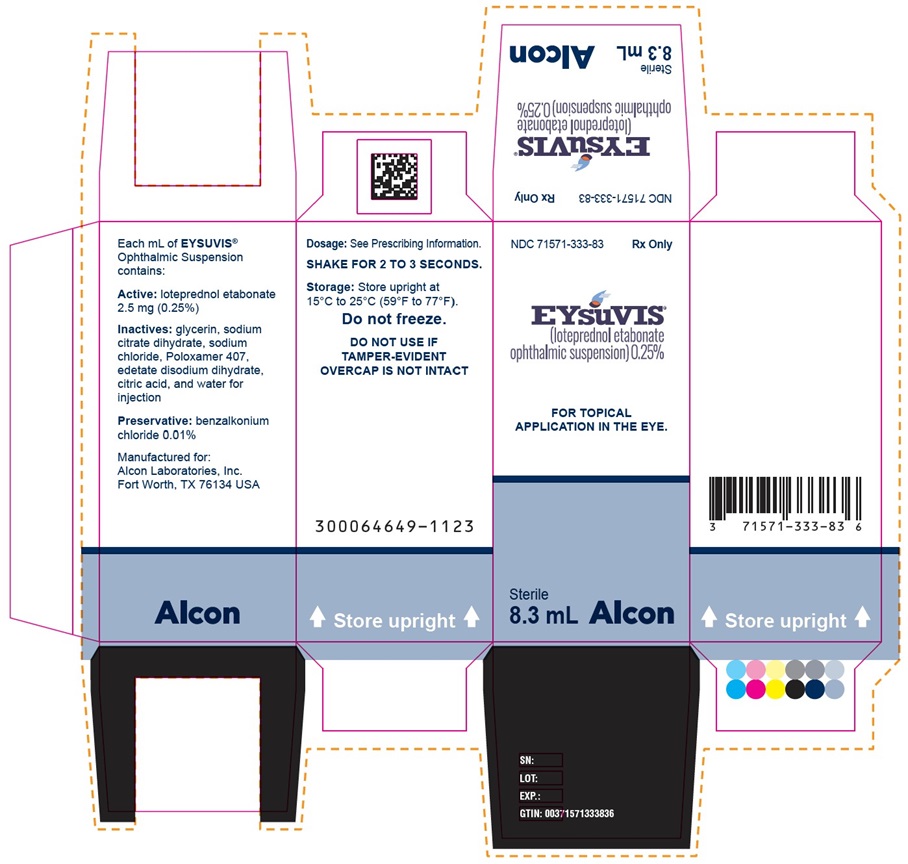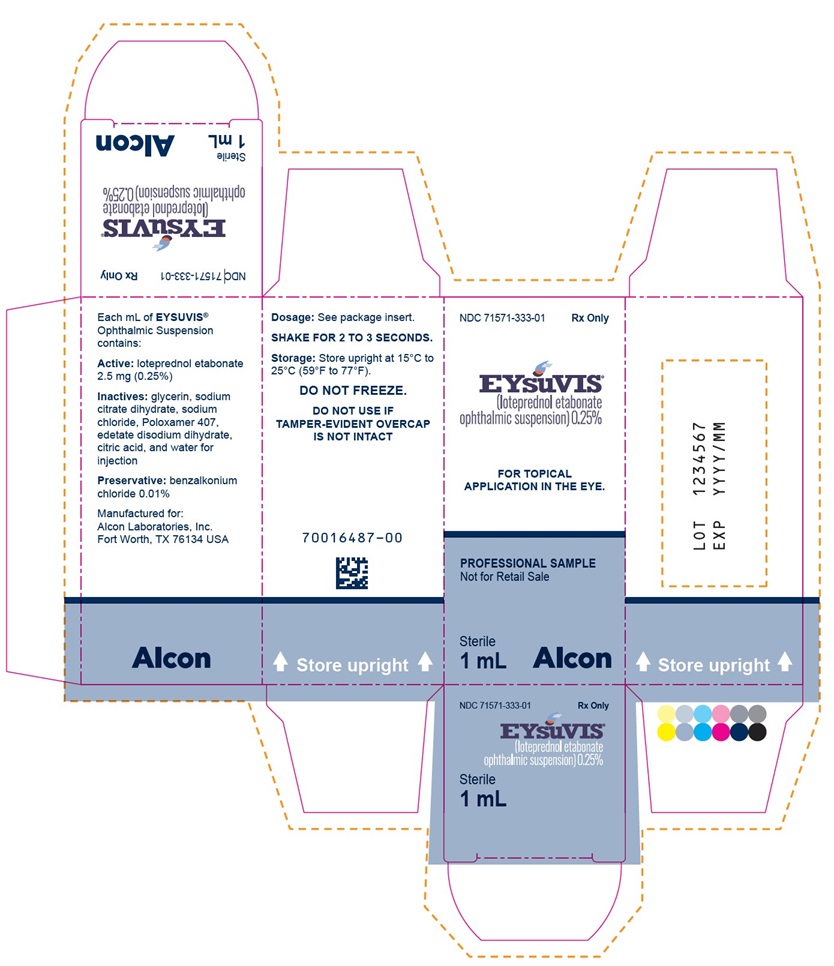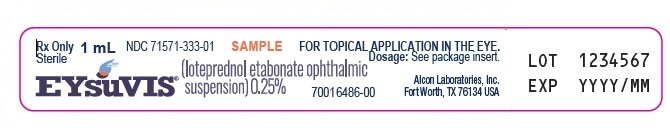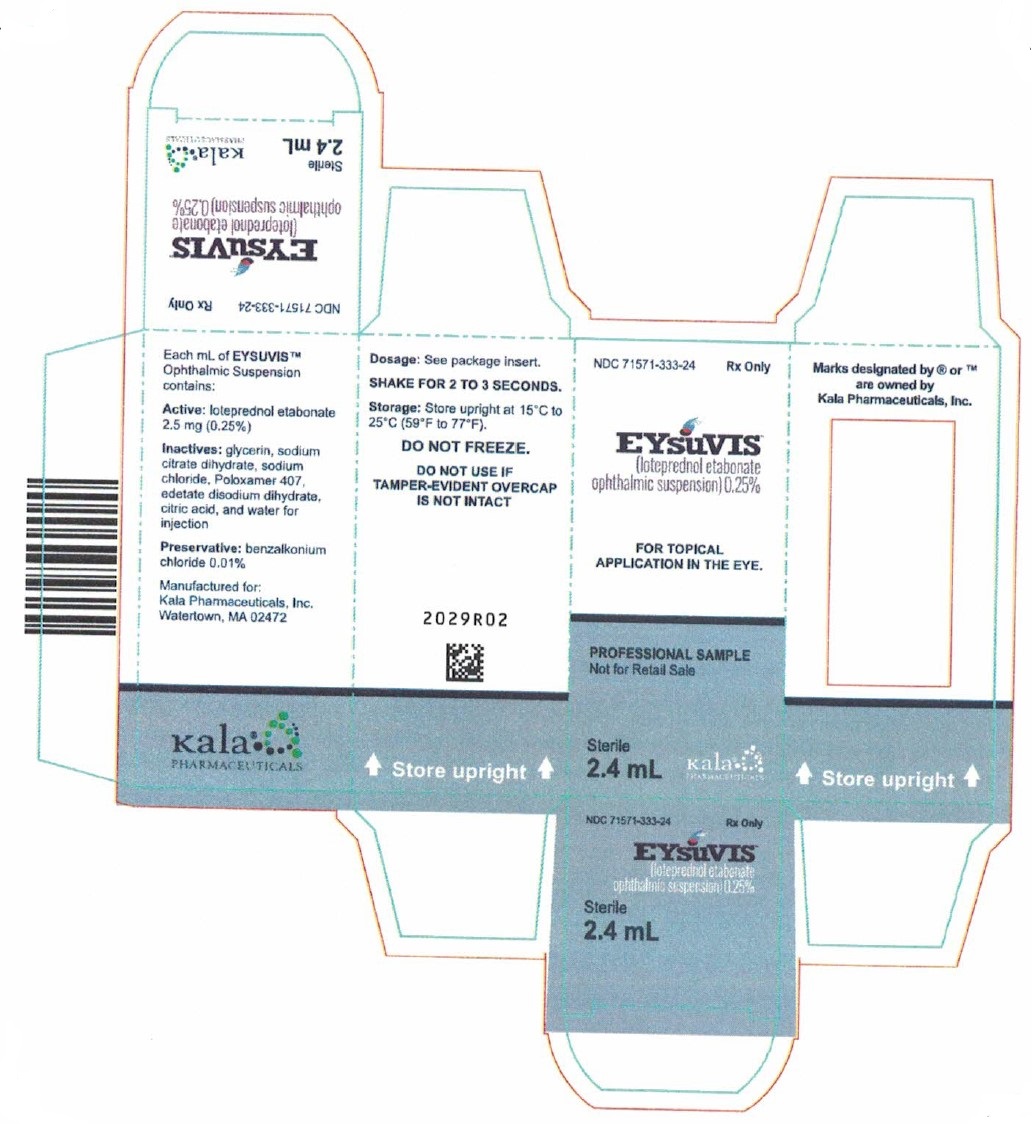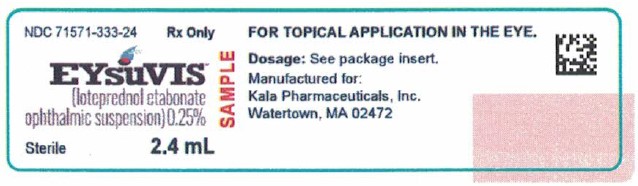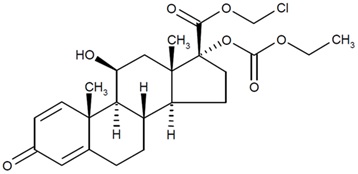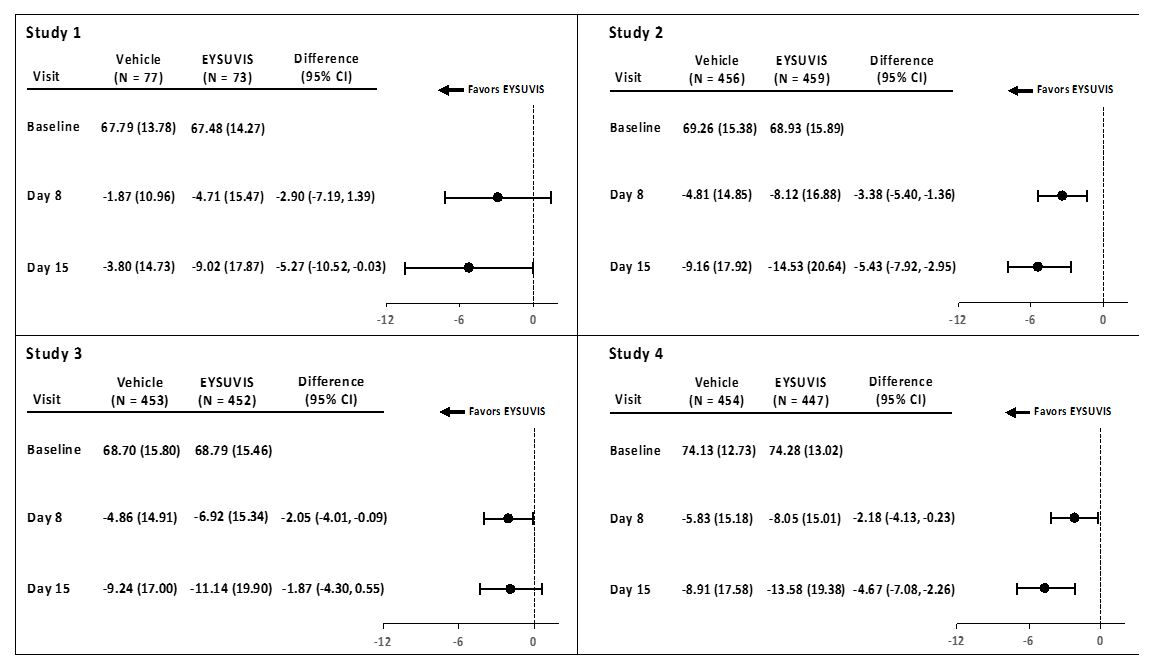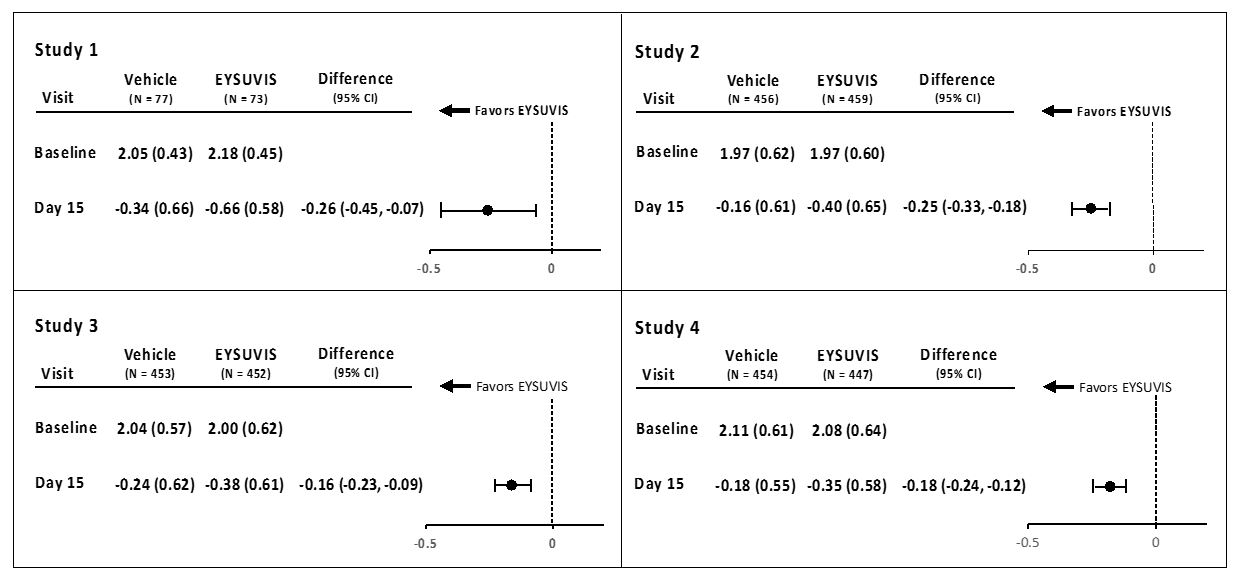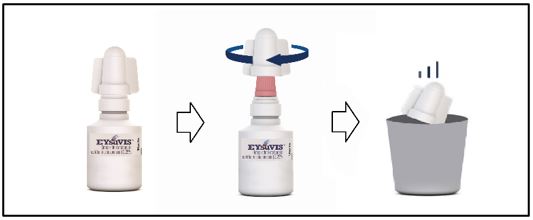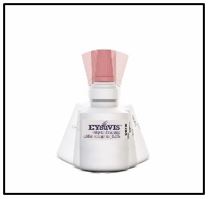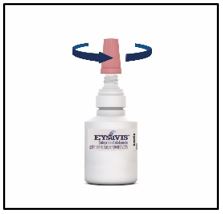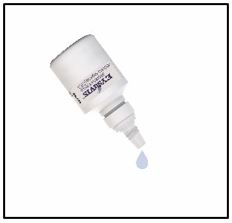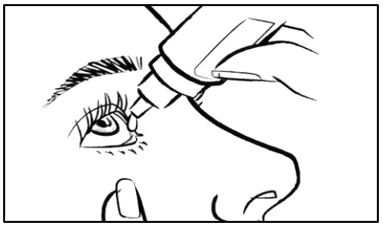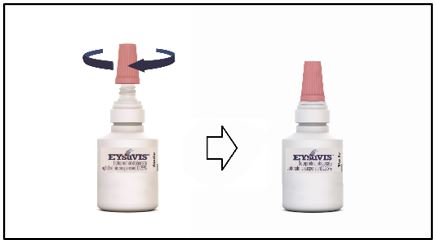 DRUG LABEL: Eysuvis
NDC: 71571-333 | Form: SUSPENSION/ DROPS
Manufacturer: ALCON LABORATORIES, INC.
Category: prescription | Type: HUMAN PRESCRIPTION DRUG LABEL
Date: 20250311

ACTIVE INGREDIENTS: LOTEPREDNOL ETABONATE 2.5 mg/1 mL

HIGHLIGHTS OF PRESCRIBING INFORMATION

These highlights do not include all the information needed to use EYSUVIS™ safely and effectively. See full prescribing information for EYSUVIS.
EYSUVIS (loteprednol etabonate ophthalmic suspension) 0.25%,
for topical ophthalmic use
Initial U.S. Approval: 1998

1 INDICATIONS AND USAGE

EYSUVIS is a corticosteroid indicated for the short-term (up to two weeks) treatment of the signs and symptoms of dry eye disease. (1)

2 DOSAGE AND ADMINISTRATION

- Shake for two to three seconds before using. (2)
- Instill one to two drops of EYSUVIS into each eye four times daily. (2)

3 DOSAGE FORMS AND STRENGTHS

Ophthalmic suspension containing 2.5 mg/mL of loteprednol etabonate. (3)

4 CONTRAINDICATIONS

EYSUVIS, as with other ophthalmic corticosteroids, is contraindicated in most viral diseases of the cornea and conjunctiva including epithelial herpes simplex keratitis (dendritic keratitis), vaccinia, and varicella, and also in mycobacterial infection of the eye and fungal diseases of ocular structures. (4)

5 WARNINGS AND PRECAUTIONS

- Delayed Healing and Corneal Perforation:The initial prescription and each renewal of the medication order should be made by a physician only after examination of the patient with the aid of magnification, such as slit lamp biomicroscopy, and, where appropriate, fluorescein staining. (5.1)
- Intraocular Pressure (IOP) Increase: Prolonged use of corticosteroids may result in glaucoma with damage to the optic nerve, defects in visual acuity and fields of vision. Renewal of the medication order should be made by a physician only after examination of the patient and evaluation of the IOP.(5.2)
- Cataracts: Use of corticosteroids may result in posterior subcapsular cataract formation. (5.3)
- Bacterial Infections: Use of corticosteroids may suppress the host response and thus increase the hazard of secondary ocular infections. In acute purulent conditions, corticosteroids may mask infection or enhance existing infection. (5.4)
- Viral Infections: Use of a corticosteroid medication in the treatment of patients with a history of herpes simplex requires great caution. Use of ocular corticosteroids may prolong the course and may exacerbate the severity of many viral infections of the eye (including herpes simplex). (5.5)
- Fungal Infections: Fungal infections of the cornea are particularly prone to develop coincidentally with long-term local corticosteroid application. Fungus invasion must be considered in any persistent corneal ulceration where a corticosteroid has been used or is in use. (5.6)

6 ADVERSE REACTIONS

The most common adverse drug reaction following the use of EYSUVIS for two weeks was instillation site pain, which was reported in 5% of patients. (6)

To report SUSPECTED ADVERSE REACTIONS, contact Alcon Laboratories, Inc. at 1-800-757-9195 or FDA at 1-800-FDA-1088 or www.fda.gov/medwatch.

FULL PRESCRIBING INFORMATION

1 INDICATIONS AND USAGE

EYSUVIS is a corticosteroid indicated for the short-term (up to two weeks) treatment of the signs and symptoms of dry eye disease.

2 DOSAGE AND ADMINISTRATION

2.1 Dosage Information

Instill one to two drops of EYSUVIS into each eye four times daily for up to two weeks. This product should only be renewed after examination under magnification such as a slit lamp and evaluation of the intraocular pressure. [see Warnings and Precautions (5.1) and (5.2)].

2.2 Administration Instructions

Instruct patient to wash hands well before each use. Shake for two to three seconds before using.

If the patient is using other eye drops in addition to EYSUVIS, advise the patient to wait at least 5 minutes between instillation of EYSUVIS and other eye drops.

If a dose is missed, take the missed dose when remembered.

3 DOSAGE FORMS AND STRENGTHS

Ophthalmic suspension containing 2.5 mg/mL of loteprednol etabonate.

4 CONTRAINDICATIONS

EYSUVIS, as with other ophthalmic corticosteroids, is contraindicated in most viral diseases of the cornea and conjunctiva including epithelial herpes simplex keratitis (dendritic keratitis), vaccinia, and varicella, and also in mycobacterial infection of the eye and fungal diseases of ocular structures.

5 WARNINGS AND PRECAUTIONS

5.1 Delayed Healing and Corneal Perforation

Topical corticosteroids have been known to delay healing and cause corneal and scleral thinning. Use of topical corticosteroids in the presence of thin corneal or scleral tissue may lead to perforation. The initial prescription and each renewal of the medication order should be made by a physician only after examination of the patient with the aid of magnification, such as slit lamp biomicroscopy, and, where appropriate, fluorescein staining.

5.2 Intraocular Pressure (IOP) Increase

Prolonged use of corticosteroids may result in glaucoma with damage to the optic nerve, as well as defects in visual acuity and fields of vision. Corticosteroids should be used with caution in the presence of glaucoma. Renewal of the medication order should be made by a physician only after examination of the patient and evaluation of the IOP.

5.3 Cataracts

Use of corticosteroids may result in posterior subcapsular cataract formation.

5.4 Bacterial Infections

Use of corticosteroids may suppress the host response and thus increase the hazard of secondary ocular infections. In acute purulent conditions of the eye, corticosteroids may mask infection or enhance existing infection.

5.5 Viral Infections

Use of corticosteroid medication in the treatment of patients with a history of herpes simplex requires great caution. Use of ocular corticosteroids may prolong the course and may exacerbate the severity of many viral infections of the eye (including herpes simplex).

5.6 Fungal Infections

Fungal infections of the cornea are particularly prone to develop coincidentally with long-term local corticosteroid application. Fungus invasion must be considered in any persistent corneal ulceration where a corticosteroid has been used or is in use. Fungal cultures should be taken when appropriate.

5.7 Risk of Contamination

Do not to allow the dropper tip to touch any surface, as this may contaminate the suspension.

5.8 Contact Lens Wear

The preservative in EYSUVIS may be absorbed by soft contact lenses. Contact lenses should be removed prior to instillation of EYSUVIS and may be reinserted 15 minutes following administration.

6 ADVERSE REACTIONS

Adverse reactions associated with ophthalmic corticosteroids include elevated intraocular pressure, which may be associated with infrequent optic nerve damage, visual acuity and field defects, posterior subcapsular cataract formation, delayed wound healing and secondary ocular infection from pathogens including herpes simplex, and perforation of the globe where there is thinning of the cornea or sclera.

6.1 Clinical Trials Experience

Because clinical trials are conducted under widely varying conditions, adverse reaction rates observed in the clinical trials of a drug cannot be directly compared to rates in the clinical trials of another drug and may not reflect the rates observed in practice.

The most common adverse reaction observed in clinical trials with EYSUVIS was instillation site pain, which was reported in 5% of patients.

8 USE IN SPECIFIC POPULATIONS

8.1 Pregnancy

Risk Summary

There are no adequate and well controlled studies with loteprednol etabonate in pregnant women. Loteprednol etabonate produced teratogenicity at clinically relevant doses in the rabbit and rat when administered orally during pregnancy. Loteprednol etabonate produced malformations when administered orally to pregnant rabbits at doses 1.4 times the recommended human ophthalmic dose (RHOD) and to pregnant rats at doses 34 times the RHOD. In pregnant rats receiving oral doses of loteprednol etabonate during the period equivalent to the last trimester of pregnancy through lactation in humans, survival of offspring was reduced at doses 3.4 times the RHOD. Maternal toxicity was observed in rats at doses 347 times the RHOD, and a maternal no observed adverse effect level (NOAEL) was established at 34 times the RHOD.

The background risk in the U.S. general population of major birth defects is 2 to 4%, and of miscarriage is 15 to 20%, of clinically recognized pregnancies.

Data

Animal Data

Embryofetal studies were conducted in pregnant rabbits administered loteprednol etabonate by oral gavage on gestation days 6 to 18, to target the period of organogenesis. Loteprednol etabonate produced fetal malformations at 0.1 mg/kg (1.4 times the recommended human ophthalmic dose (RHOD) based on body surface area, assuming 100% absorption). Spina bifida (including meningocele) was observed at 0.1 mg/kg, and exencephaly and craniofacial malformations were observed at 0.4 mg/kg (5.6 times the RHOD). At 3 mg/kg (41 times the RHOD), loteprednol etabonate was associated with increased incidences of abnormal left common carotid artery, limb flexures, umbilical hernia, scoliosis, and delayed ossification. Abortion and embryofetal lethality (resorption) occurred at 6 mg/kg (83 times the RHOD). A NOAEL for developmental toxicity was not established in this study. The NOAEL for maternal toxicity in rabbits was 3 mg/kg/day.

Embryofetal studies were conducted in pregnant rats administered loteprednol etabonate by oral gavage on gestation days 6 to 15, to target the period of organogenesis. Loteprednol etabonate produced fetal malformations, including absent innominate artery at 5 mg/kg (34 times the RHOD); and cleft palate, agnathia, cardiovascular defects, umbilical hernia, decreased fetal body weight and decreased skeletal ossification at 50 mg/kg (347 times the RHOD). Embryofetal lethality (resorption) was observed at 100 mg/kg (695 times the RHOD). The NOAEL for developmental toxicity in rats was 0.5 mg/kg (3.4 times the RHOD). Loteprednol etabonate was maternally toxic (reduced body weight gain) at 50 mg/kg/day. The NOAEL for maternal toxicity was 5 mg/kg.

A peri-/postnatal study was conducted in rats administered loteprednol etabonate by oral gavage from gestation day 15 (start of fetal period) to postnatal day 21 (the end of lactation period). At 0.5 mg/kg (3.4 times the clinical dose), reduced survival was observed in live-born offspring. Doses ≥ 5 mg/kg (34 times the RHOD) caused umbilical hernia/incomplete gastrointestinal tract. Doses ≥ 50 mg/kg (347 times the RHOD) produced maternal toxicity (reduced body weight gain, death), decreased number of live-born offspring, decreased birth weight, and delays in postnatal development. A developmental NOAEL was not established in this study. The NOAEL for maternal toxicity was 5 mg/kg.

8.2 Lactation

There are no data on the presence of loteprednol etabonate in human milk, the effects on the breastfed infant, or the effects on milk production. The developmental and health benefits of breastfeeding should be considered, along with the mother's clinical need for EYSUVIS and any potential adverse effects on the breastfed infant from EYSUVIS.

8.4 Pediatric Use

Safety and effectiveness in pediatric patients have not been established.

8.5 Geriatric Use

No overall differences in safety and effectiveness have been observed between elderly and younger adult patients.

11 DESCRIPTION

Loteprednol etabonate is a corticosteroid. Its chemical name is chloromethyl 17α-[(ethoxycarbonyl)oxy]-11β-hydroxy-3-oxoandrosta-1,4-diene-17β-carboxylate. Its molecular formula is C24H31ClO7 and its chemical structure is:

C24H31ClO7
Mol. Wt. 467.0

EYSUVIS (loteprednol etabonate ophthalmic suspension) 0.25% contains a sterile, topical anti-inflammatory corticosteroid for ophthalmic use. Each mL contains:

- ACTIVE: loteprednol etabonate 2.5 mg (0.25%)
- INACTIVES: glycerin, sodium citrate dihydrate, sodium chloride, Poloxamer 407, edetate disodium dihydrate, citric acid, and water for injection.
- PRESERVATIVE: benzalkonium chloride 0.01%

12 CLINICAL PHARMACOLOGY

12.1 Mechanism of Action

Corticosteroids inhibit the inflammatory response to a variety of inciting agents and delay or slow healing. Corticosteroids inhibit the edema, fibrin deposition, capillary dilation, leukocyte migration, capillary proliferation, fibroblast proliferation, deposition of collagen, and scar formation associated with inflammation. While glucocorticoids are known to bind to and activate the glucocorticoid receptor, the molecular mechanisms involved in glucocorticoid/glucocorticoid receptor-dependent modulation of inflammation are not clearly established. However, corticosteroids are thought to inhibit prostaglandin production.

12.3 Pharmacokinetics

Loteprednol etabonate is lipid soluble and can penetrate into cells. Loteprednol etabonate is synthesized through structural modifications of prednisolone-related compounds so that it will undergo a predictable transformation to an inactive metabolite. Based upon in vivo and in vitro preclinical metabolism studies, loteprednol etabonate undergoes extensive metabolism to inactive carboxylic acid metabolites, PJ-91 and PJ-90.

Following bilateral topical ocular dosing of two drops of EYSUVIS four times a day for 14 days in 20 healthy adult subjects, the plasma concentrations of loteprednol etabonate were below the limit of quantitation (1 ng/mL) at all timepoints.

13 NONCLINICAL TOXICOLOGY

13.1 Carcinogenesis, Mutagenesis, Impairment of Fertility

Long-term animal studies have not been conducted to evaluate the carcinogenic potential of loteprednol etabonate. Loteprednol etabonate was not genotoxic in vitro in the Ames test, the mouse lymphoma thymidine kinase (tk) assay, in a chromosome aberration test in human lymphocytes, or in vivo in the single dose mouse micronucleus assay. Treatment of male and female rats with 25 mg/kg/day of loteprednol etabonate (174 times the RHOD based on body surface area, assuming 100% absorption) prior to and during mating caused pre-implantation loss and decreased the number of live fetuses/live births. The NOAEL for fertility in rats was 5 mg/kg/day (34 times the RHOD).

14 CLINICAL STUDIES

The safety and efficacy of EYSUVIS for the treatment of dry eye disease was assessed in approximately 2900 patients with dry eye disease. Patients received either EYSUVIS or vehicle (1:1 ratio) four times a day for 2 weeks in 4 multi-centered, randomized, double-masked, placebo-controlled trials. The use of artificial tears was not allowed during the trials.

Effects on Symptoms of Dry Eye Disease

Ocular discomfort severity (ODS) was rated by patients daily over the course of the trial using a visual analog scale (0 = very mild, 100 = very severe). A larger reduction in ocular discomfort severity favoring EYSUVIS was observed at Day 15 in the patient population (see Figure 1).

Figure 1: Mean Change (SD) from Baseline and Treatment Difference (EYSUVIS-
Vehicle) in Ocular Discomfort Severity Score in Patients with Dry Eye Disease

Treatment differences between the EYSUVIS and vehicle groups are displayed for each study, based on least square means and 2-sided confidence intervals for the change from baseline.

Effects on Signs of Dry Eye Disease

Conjunctival hyperemia was graded using the Cornea and Contact Lens Research Unit (CCLRU) grading scale (0 = none; 1 = very slight; 2 = slight; 3 = moderate; 4 = severe). A larger reduction in hyperemia favoring EYSUVIS was observed at Day 15 in all four trials (Figure 2).

Figure 2: Mean Change (SD) from Baseline and Treatment Difference (EYSUVIS-
Vehicle) in Conjunctival Hyperemia in Patients with Dry Eye Disease

Treatment differences between the EYSUVIS and vehicle groups are displayed for each study, based on least square means and 2-sided confidence intervals for the change from baseline.

16 HOW SUPPLIED/STORAGE AND HANDLING

EYSUVIS (loteprednol etabonate ophthalmic suspension) 0.25% is a sterile ophthalmic suspension. It is supplied in a white, low-density polyethylene dropper bottle with a linear low-density polyethylene tip, a pink high-density polyethylene cap, and a white low-density polyethylene tamper-evident overcap in the following size:

8.3 mL in a 10 mL bottle (NDC 71571-333-83)

Storage and Handling

Do not use if tamper-evident overcap seal is not intact.

The white tamper-evident overcap can be thrown away. Retain the pink cap and keep the bottle tightly closed when not in use.

Store upright at 15°C to 25°C (59°F to 77°F). Do not freeze. After opening, EYSUVIS can be used until the expiration date on the bottle.

17 PATIENT COUNSELING INFORMATION

Advise the patient to read the FDA-approved patient labeling (Instructions for Use).

Administration

Instruct the patient to shake the bottle for two to three seconds before using. If a dose is missed, take the missed dose when remembered.

Corneal Status and Intraocular Pressure Monitoring

The initial prescription and each renewal of the medication order should be made only after evaluation of the intraocular pressure and examination of the patient with the aid of magnification, such as slit-lamp biomicroscopy.

Risk of Contamination

Advise patients to wash their hands well before each use. Advise patients not to allow the dropper tip to touch any surface, as this may contaminate the suspension.

Risk of Secondary Infection

Advise the patient to consult a physician, if pain develops, redness, itching, or inflammation becomes aggravated.

Contact Lens Wear

Advise patients that the preservative in EYSUVIS may be absorbed by soft contact lenses. Contact lenses should be removed prior to instillation of EYSUVIS and may be reinserted 15 minutes following administration.

Manufactured for:
Alcon Laboratories, Inc.
Fort Worth, Texas 76134 USA
Part # 70016481-00
U.S. Pat.: www.alconpatents.com
© 2023 Alcon Inc.
Alcon

INSTRUCTIONS FOR USE

EYSUVIS [eye-SU-vis]
(loteprednol etabonate ophthalmic suspension) 0.25%
for topical ophthalmic use

This Instructions for Use contains information on how to properly administer EYSUVIS.

Important Information You Need to Know Before Using EYSUVIS

- EYSUVIS is for use in the eye.
- Wash your hands before using EYSUVIS.
- Do not use if the tamper-evident seal is not intact.
- Do not let the EYSUVIS dropper tip touch your eye, fingers, or any other surfaces to avoid contamination or injury to your eye.
- Use EYSUVIS exactly as your doctor tells you to.
- If you are using EYSUVIS with other eye (ophthalmic) medicines, you should wait at least 5 minutes between using EYSUVIS and the other medicine.
- If you wear contact lenses, remove them before using EYSUVIS.
- Put the pink cap back on EYSUVIS after each use.

Before you use EYSUVIS for the first time:

There are two caps on your bottle of EYSUVIS. Hold the bottle firmly by its neck. Remove the white cap by twisting it clockwise (See Figure A). Throw away the white cap. EYSUVIS is now ready to use.

Figure A

Follow Steps 1 to 6 each time you use EYSUVIS.

1. Wash your hands well.
2. Shake the EYSUVIS bottle for 2 to 3 seconds before using (See Figure B).
  Figure B
3. Remove the pink cap from the top of the EYSUVIS dropper by turning it counterclockwise (See Figure C). Keep the pink cap. Do not let the EYSUVIS dropper tip touch your eye, fingers, or any other surface.
  Figure C
4. Turn the EYSUVIS bottle upside down (See Figure D).
  Figure D
5. Tilt your head back. Hold the bottle directly above your affected eye. Squeeze the middle of the EYSUVIS bottle gently to put 1 to 2 drops (follow your doctor's instruction) into the affected eye (See Figure E).
  Figure E
6. Place the pink cap back onto the EYSUVIS bottle and tighten by turning clockwise (See Figure F).
  Figure F

If you use contact lenses, wait for 15 minutes before placing them back in.

How should I store EYSUVIS?

- Store EYSUVIS upright between 59ºF to 77ºF (15ºC to 25ºC).
- Do not freeze.
- After opening, EYSUVIS can be used until the expiration date (EXP) on the bottle. The expiration date can be found on the lower right side of the label on the bottle.

Keep EYSUVIS and all medicines out of the reach of children.

This Instructions for Use has been approved by the U.S. Food and Drug Administration.

Manufactured for:
Alcon Laboratories, Inc.
Fort Worth, Texas 76134 USA
Approved 11/2023

PRINCIPAL DISPLAY PANEL - NDC: 71571-333-83 - Bottle Label

NDC 71571-333-83 Rx Only
EYsuVIS®
(loteprednol etabonate
ophthalmic suspension) 0.25%
Sterile
8.3 mL
FOR TOPICAL APPLICATION
IN THE EYE.
Dosage: See Prescribing Information.
Manufactured for: Alcon Laboratories, Inc.
Fort Worth, TX 76134 USA

PRINCIPAL DISPLAY PANEL - NDC: 71571-333-83 - Carton Label

NDC 71571-333-83 Rx Only
EYsuVIS®
(loteprednol etabonate
ophthalmic suspension) 0.25%
FOR TOPICAL APPLICATION
IN THE EYE.
Sterile
8.3 mL
Alcon
Dosage: See Prescribing Information.
SHAKE FOR 2 TO 3 SECONDS
Storage: Store upright at
15°C to 25°C (59°F to 77°F).
Do not freeze.
DO NOT USE IF
TAMPER-EVIDENT
OVERCAP IS NOT INTACT
300064649-1123
Store Upright
Manufactured for:
Alcon Laboratories, Inc.
Fort Worth, TX 76134 USA